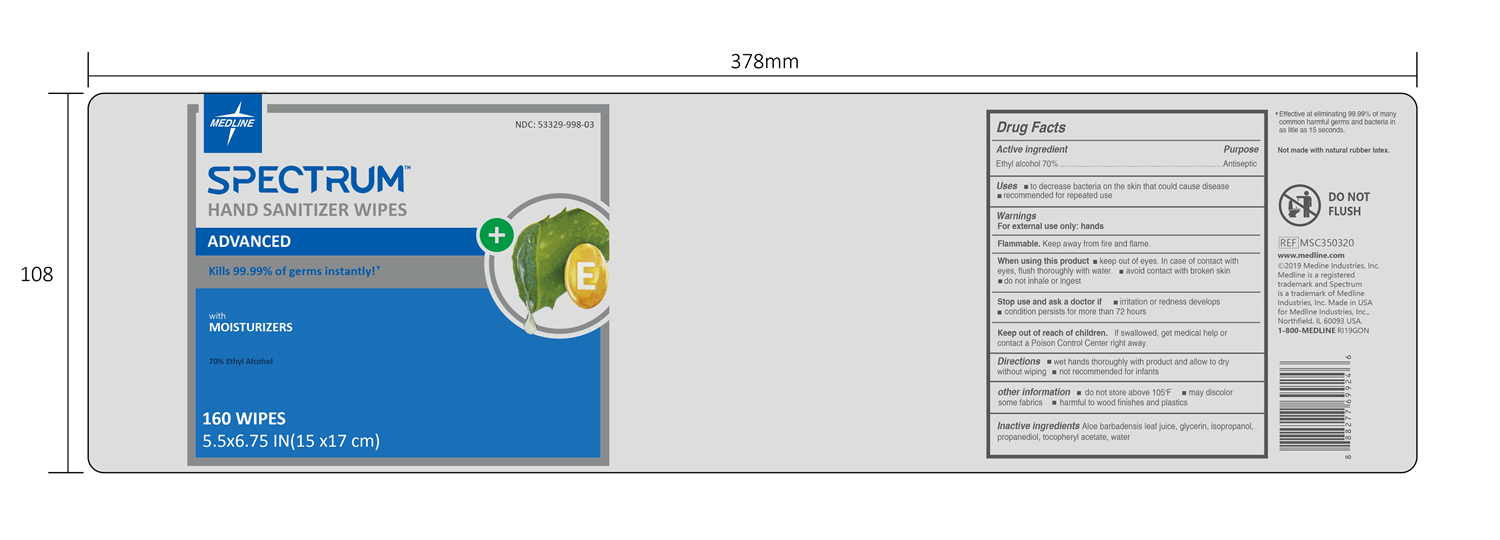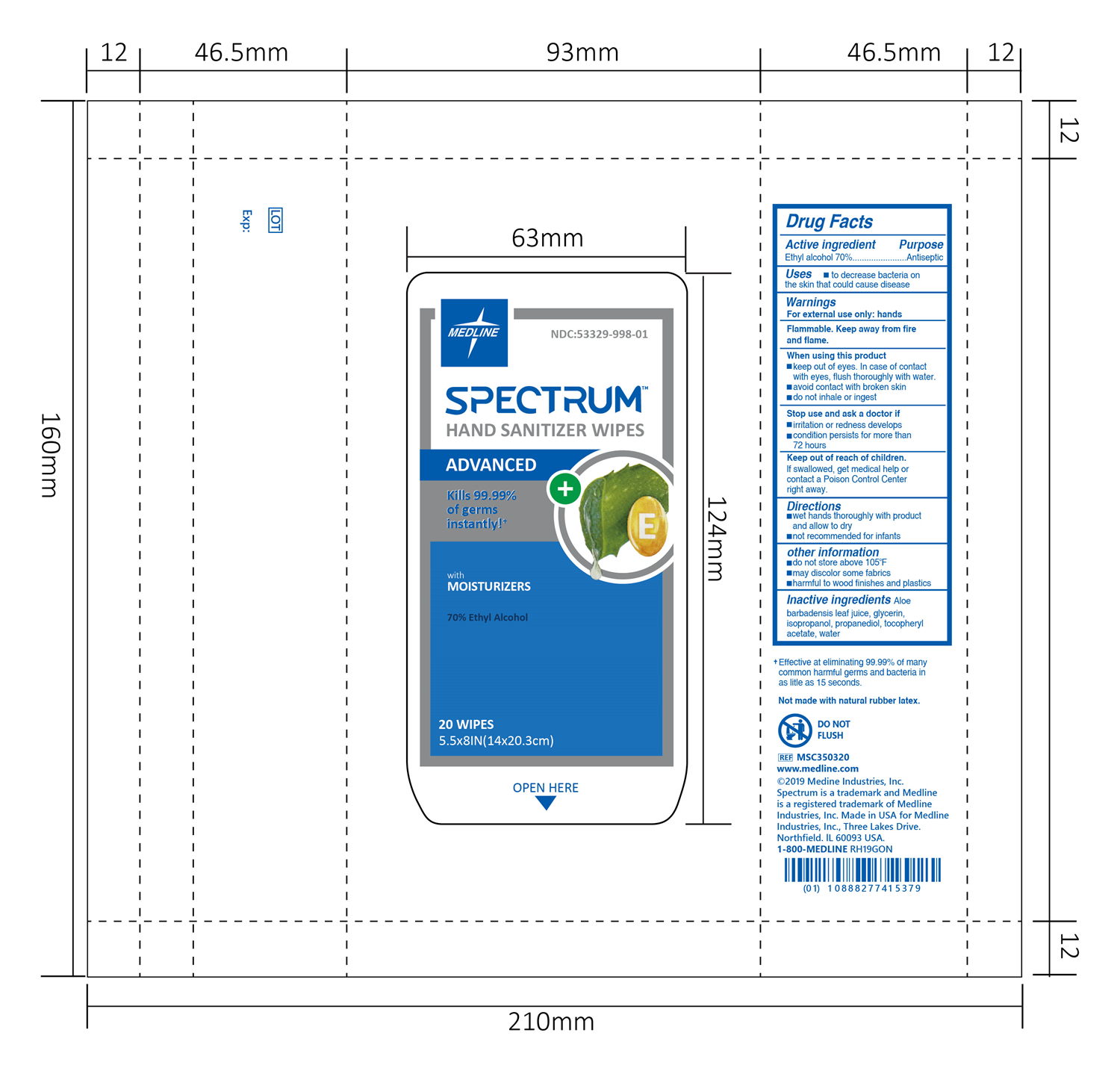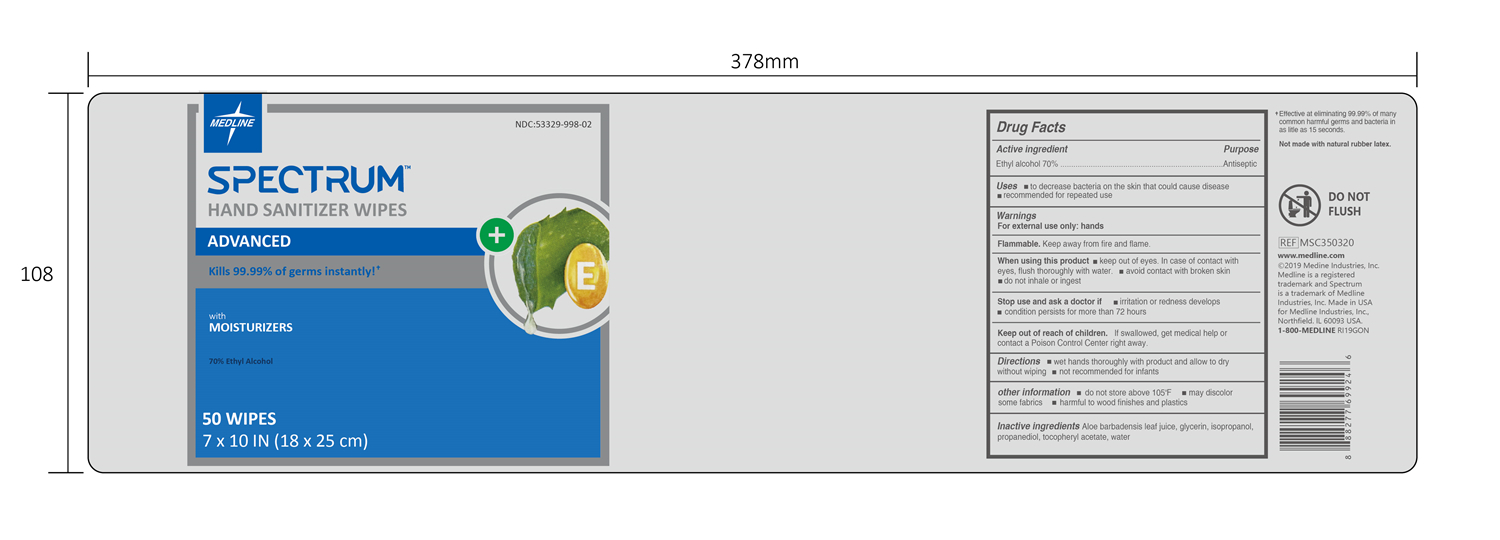 DRUG LABEL: SPECTRUM HAND SANITIZER WIPES
NDC: 53329-998 | Form: CLOTH
Manufacturer: Medline Industries, Inc.
Category: otc | Type: HUMAN OTC DRUG LABEL
Date: 20231027

ACTIVE INGREDIENTS: ALCOHOL 70 mL/100 mL
INACTIVE INGREDIENTS: PROPANEDIOL; GLYCERIN; ALOE VERA LEAF; .ALPHA.-TOCOPHEROL ACETATE; ISOPROPYL ALCOHOL; WATER

SPECTRUM HAND SANITIZER WIPES

Active ingredient

Ethyl alcohol 70%

Purpose

Antiseptic

Uses

to decrease bacteria on the skin that could cause disease

Warnings

For external use only: hands

Flammable. Keep away from fire and flame.

When using this product

keep out of eyes. In case of contact with eyes, flush thoroughly with water.
avoid contact with broken skin
do not inhale or ingest

Stop use and ask a doctor if

irritation or redness develops
condition persists for more than 72 hours

Keep out of reach of children.

If swallowed, get medical help or contact a Poison Control Center right away.

Directions

wet hands thoroughly with product and allow to dry

not recommended for infants

other information

do not store above 105ºF
may discolor some fabrics
harmful to wood finishes and plastics

Inactive ingredients

Aloe barbadensis leaf juice, glycerin, isopropanol, propanediol, tocopheryl acetate, water

Uses

to decrease bacteria on the skin that could cause disease

recommended for repeated use

Directions

wet hands thoroughly with product and allow to dry without wiping
not recommended for infants

PACKAGE LABEL

20 WIPES, NDC: 53329-998-01

PACKAGE LABEL

50 WIPES, NDC: 53329-998-02

PACKAGE LABEL

160 WIPES, NDC: 53329-998-03